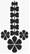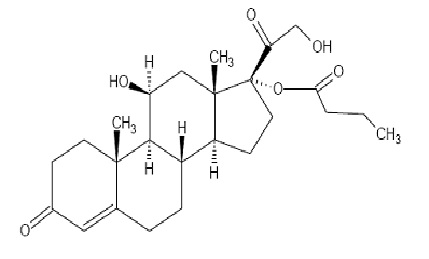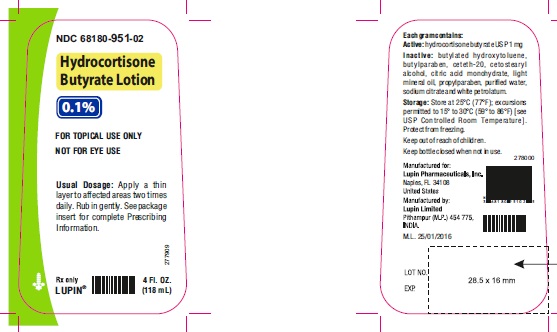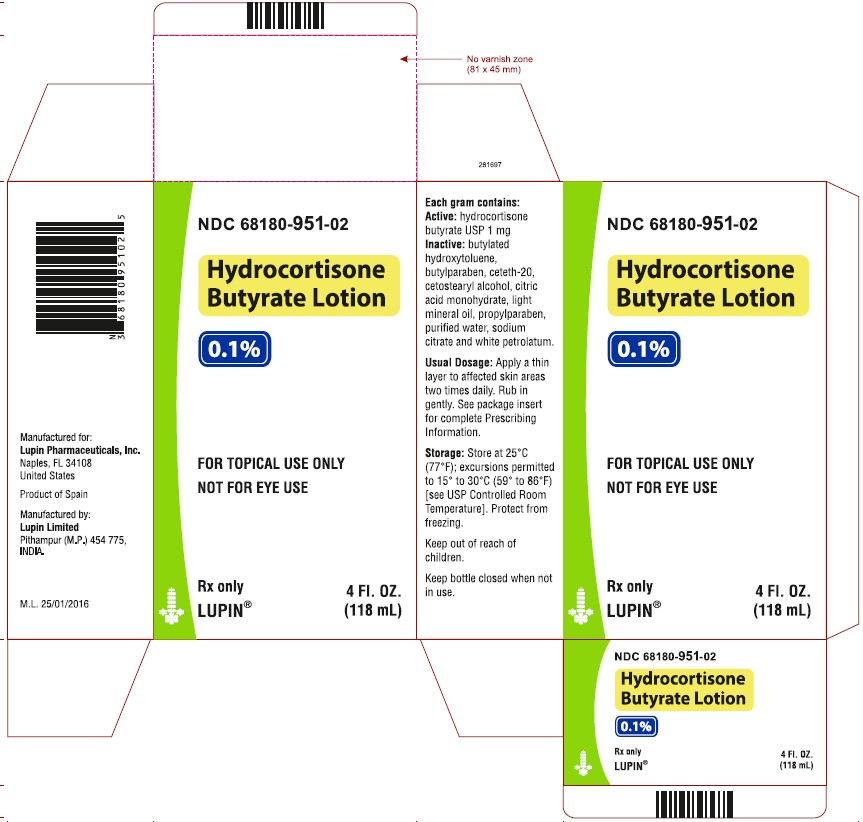 DRUG LABEL: Hydrocortisone Butyrate
NDC: 68180-951 | Form: LOTION
Manufacturer: Lupin Pharmaceuticals, Inc.
Category: prescription | Type: HUMAN PRESCRIPTION DRUG LABEL
Date: 20251013

ACTIVE INGREDIENTS: HYDROCORTISONE BUTYRATE 1 mg/1 mL
INACTIVE INGREDIENTS: BUTYLATED HYDROXYTOLUENE; BUTYLPARABEN; CETETH-20; CETOSTEARYL ALCOHOL; CITRIC ACID MONOHYDRATE; LIGHT MINERAL OIL; PROPYLPARABEN; WATER; SODIUM CITRATE; PETROLATUM

HIGHLIGHTS OF PRESCRIBING INFORMATION

These highlights do not include all the information needed to use HYDROCORTISONE BUTYRATE LOTION, safely and effectively. See full prescribing information for HYDROCORTISONE BUTYRATE LOTION.
HYDROCORTISONE BUTYRATE lotion, for topical use
Initial U.S. Approval: 1982

1 INDICATIONS AND USAGE

Hydrocortisone butyrate lotion, 0.1% is a corticosteroid indicated for the topical treatment of mild to moderate atopic dermatitis in patients 3 months of age and older. (1)

2 DOSAGE AND ADMINISTRATION

- Apply a thin layer to the affected skin two times daily. (2)
- Rub in gently. (2)
- Discontinue hydrocortisone butyrate lotion, 0.1% when control is achieved. (2)
- Reassess diagnosis if no improvement is seen within 2 weeks. Before prescribing for more than 2 weeks, any additional benefits of extending treatment to 4 weeks should be weighed against the risk of HPA axis suppression and local adverse events. Safety and efficacy of hydrocortisone butyrate lotion, 0.1% has not been established beyond 4 weeks of use. (2)
- Avoid use under occlusion or in the diaper area. (2)
- Hydrocortisone butyrate lotion, 0.1% is not for oral, ophthalmic, or intravaginal use. (2)

3 DOSAGE FORMS AND STRENGTHS

Lotion, 0.1% (1 mg/g), supplied in bottles of 2 fl. oz. and 4 fl. oz. (3)

4 CONTRAINDICATIONS

None. (4)

5 WARNINGS AND PRECAUTIONS

- Reversible hypothalamic-pituitary-adrenal (HPA) axis suppression may occur, with the potential for glucocorticosteroid insufficiency. Consider periodic evaluations for HPA axis suppression if hydrocortisone butyrate lotion is applied to large surface areas or used under occlusion. If HPA axis suppression is noted, reduce the application frequency, discontinue use, or switch to a lower potency corticosteroid. (5.1, 8.4)
- Systemic effects of topical corticosteroids may also include manifestations of Cushing's syndrome, hyperglycemia, and glucosuria. (5.1, 8.4)
- Pediatric patients may be more susceptible to systemic toxicity due to their larger skin surface-to-body-mass ratios. (5.1, 8.4)
- Initiate appropriate therapy if concomitant skin infections develop. (5.2)

6 ADVERSE REACTIONS

The most common adverse reactions (>1%) are application site reactions. (6)

To report SUSPECTED ADVERSE REACTIONS, contact Lupin Pharmaceuticals, Inc. at 1-800-399-2561 and/or FDA at 1-800-FDA-1088 or www.fda.gov/medwatch.

FULL PRESCRIBING INFORMATION

1 INDICATIONS AND USAGE

Hydrocortisone butyrate lotion, 0.1% is indicated for the topical treatment of mild to moderate atopic dermatitis in patients 3 months of age and older.

2 DOSAGE AND ADMINISTRATION

Apply a thin layer to the affected skin areas two times daily, and rub in gently. Do not apply hydrocortisone butyrate lotion, 0.1% in the diaper area unless directed by a physician.

Discontinue therapy when control is achieved. If no improvement is seen within 2 weeks, reassessment of the diagnosis may be necessary. Before prescribing for more than 2 weeks, any additional benefits of extending treatment to 4 weeks should be weighed against the risk of HPA axis suppression and local adverse events. The safety and efficacy of hydrocortisone butyrate lotion, 0.1% has not been established beyond 4 weeks of use [see WARNINGS AND PRECAUTIONS (5.1)].

Do not use hydrocortisone butyrate lotion, 0.1% with occlusive dressings unless directed by a physician. Avoid use in the diaper area, as diapers or plastic pants may constitute occlusive dressings.

Hydrocortisone butyrate lotion, 0.1% is not for oral, ophthalmic, or intravaginal use.

3 DOSAGE FORMS AND STRENGTHS

Lotion, 0.1%. Each gram of hydrocortisone butyrate lotion, 0.1% contains 1 mg of hydrocortisone butyrate USP in a white to off white lotion base. Hydrocortisone butyrate lotion, 0.1% is supplied in bottles of 2 fl. oz. and 4 fl. oz.

4 CONTRAINDICATIONS

None.

5 WARNINGS AND PRECAUTIONS

5.1 Hypothalamic-Pituitary-Adrenal (HPA) Axis Suppression

Systemic effects of topical corticosteroids may include reversible HPA axis suppression, manifestations of Cushing's syndrome, hyperglycemia, and glucosuria.

Studies conducted in pediatric subjects demonstrated reversible HPA axis suppression after use of hydrocortisone butyrate lotion. Pediatric patients may be more susceptible than adults to systemic toxicity from equivalent doses of hydrocortisone butyrate lotion due to their larger skin surface-to-body mass ratios [see USE IN SPECIFIC POPULATIONS (8.4)].

Patients applying a topical corticosteroid to a large surface area or to areas under occlusion should be considered for periodic evaluation of the HPA axis. This may be done by using cosyntropin (ACTH1 to 24) stimulation testing (CST).

Minimize systemic corticosteroid effects by mitigating the risk factors for increased systemic absorption and using hydrocortisone butyrate lotion as recommended [see DOSAGE AND ADMINISTRATION (2)].

If HPA axis suppression is noted, the frequency of application should be reduced or the drug should be withdrawn, or a less potent corticosteroid should be substituted. Signs and symptoms of glucocorticosteroid insufficiency may occur, requiring supplemental systemic corticosteroids [see ADVERSE REACTIONS (6)].

5.2 Concomitant Skin Infections

If skin infections are present or develop, an appropriate antifungal, antibacterial or antiviral agent should be used. If a favorable response does not occur promptly, use of hydrocortisone butyrate lotion should be discontinued until the infection has been adequately controlled [see ADVERSE REACTIONS (6)].

5.3 Allergic Contact Dermatitis

Allergic contact dermatitis with corticosteroids is usually diagnosed by observing a failure to heal rather than noticing a clinical exacerbation. Such an observation should be corroborated with appropriate patch testing. Discontinue hydrocortisone butyrate lotion if the diagnosis is established [see ADVERSE REACTIONS (6)].

6 ADVERSE REACTIONS

The following adverse reactions are discussed in greater detail in other sections of the labeling:

- HPA axis suppression. This has been observed in pediatric subjects using hydrocortisone butyrate lotion [see WARNINGS AND PRECAUTIONS (5.1) and USE IN SPECIFIC POPULATIONS (8.4)]
- Concomitant skin infections [see WARNINGS AND PRECAUTIONS (5.2)]
- Allergic contact dermatitis [ see WARNINGS AND PRECAUTIONS (5.3)]

6.1 Clinical Trials Experience

Because clinical trials are conducted under widely varying conditions, the adverse reaction rates observed cannot be directly compared to rates in other clinical trials and may not reflect the rates observed in clinical practice.

The safety data derived from hydrocortisone butyrate lotion clinical trials reflect exposure to hydrocortisone butyrate lotion twice daily for up to four weeks in separate clinical trials involving pediatric subjects 3 months to 18 years of age and adult subjects 18 years of age and older with mild to moderate atopic dermatitis.

Adverse reactions shown in the tables below include those for which there is some basis to believe there is a causal relationship to hydrocortisone butyrate lotion. Although the rates of application site reactions in the vehicle group were greater than those in the hydrocortisone butyrate lotion group in both studies, these rates are included in the tables (Table 1 and Table 2) because skin irritation is a known adverse reaction of topical corticosteroids.

TABLE 1. Frequency of adverse reactions in pediatric subjects with mild to moderate atopic dermatitis
 | Hydrocortisone Butyrate Lotion (n=139) n (%) | Vehicle (n=145) n (%)
Application site reactions, including application site burning, pruritus, dermatitis, erythema, eczema, inflammation, or irritation | 2 (1) | 20 (14)
Infantile acne | 1 (1) | 0 (0)
Skin depigmentation | 1 (1) | 0 (0)

TABLE 2. Frequency of adverse reactions in adult subjects with mild to moderate atopic dermatitis
 | Hydrocortisone Butyrate Lotion (n=151) n (%) | Vehicle (n=150) n (%)
Application site reactions, including application site burning, dermatitis, eczema, erythema, or pruritus | 5 (3) | 7 (5)

6.2 Postmarketing Experience

Because adverse reactions are reported voluntarily from a population of uncertain size, it is not always possible to reliably estimate their frequency or establish a causal relationship to drug exposure.

The following additional local adverse reactions have been reported infrequently with topical corticosteroids, and they may occur more frequently with the use of occlusive dressings and higher potency corticosteroids. These reactions included: irritation, folliculitis, acneiform eruptions, hypopigmentation, perioral dermatitis, allergic contact dermatitis, secondary infection, skin atrophy, striae, miliaria and telangiectasia.

8 USE IN SPECIFIC POPULATIONS

8.1 Pregnancy

Pregnancy Category C.

There are no adequate and well-controlled studies in pregnant women. Therefore, hydrocortisone butyrate lotion should be used during pregnancy only if the potential benefit justifies the potential risk to the fetus.

Corticosteroids have been shown to be teratogenic in laboratory animals when administered systemically at relatively low dosage levels. Some corticosteroids have been shown to be teratogenic after dermal application in laboratory animals.

Note: The animal multiples of human exposure calculations in this label were based on body surface area comparisons for an adult (i.e., mg/m^2/day dose comparisons) assuming 100% human percutaneous absorption of a maximum topical human dose (MTHD) for hydrocortisone butyrate lotion (25 g lotion).

Systemic embryofetal development studies were conducted in rats and rabbits.

Subcutaneous doses of 0.6, 1.8 and 5.4 mg/kg/day hydrocortisone butyrate were administered to pregnant female rats during gestation days 6 to 17. In the presence of maternal toxicity, fetal effects noted at 5.4 mg/kg/day (2X MTHD) included an increased incidence of ossification variations and unossified sternebra. No treatment-related effects on embryofetal toxicity or teratogenicity were noted at doses of 5.4 mg/kg/day and 1.8 mg/kg/day, respectively (2X MTHD and 0.7X MTHD, respectively).

Subcutaneous doses of 0.1, 0.2 and 0.3 mg/kg/day hydrocortisone butyrate were administered to pregnant female rabbits during gestation days 7 to 20. An increased incidence of abortion was noted at 0.3 mg/kg/day (0.2X MTHD). In the absence of maternal toxicity, a dose-dependent decrease in fetal body weight was noted at doses ≥0.1 mg/kg/day (0.1X MTHD). Additional indicators of embryofetal toxicity (reduction in litter size, decreased number of viable fetuses, increased post-implantation loss) were noted at doses ≥0.2 mg/kg/day (0.2X MTHD). Additional fetal effects noted in this study included delayed ossification noted at doses ≥0.1 mg/kg/day and an increased incidence of fetal malformations (primarily skeletal malformations) noted at doses ≥0.2 mg/kg/day. A dose at which no treatment-related effects on embryofetal toxicity or teratogenicity were observed was not established in this study.

Additional systemic embryofetal development studies were conducted in rats and mice. Subcutaneous doses of 0.1 and 9 mg/kg/day hydrocortisone butyrate were administered to pregnant female rats during gestation days 9 to 15. In the presence of maternal toxicity, an increase in fetal deaths and fetal resorptions and an increase in the number of ossifications in caudal vertebrae were noted at a dose of 9 mg/kg/day (3X MTHD). No treatment-related effects on embryofetal toxicity or teratogenicity were noted at 0.1 mg/kg/day (0.1X MTHD).

Subcutaneous doses of 0.2 and 1 mg/kg/day hydrocortisone butyrate were administered to pregnant female mice during gestation days 7 to 13. In the absence of maternal toxicity, an increased number of cervical ribs and one fetus with clubbed legs were noted at a dose of 1 mg/kg/day (0.2X MTHD). No treatment-related effects on embryofetal toxicity or teratogenicity were noted at doses of 1 and 0.2 mg/kg/day, respectively (0.2X MTHD and 0.1X MTHD, respectively).

No topical embryofetal development studies were conducted with hydrocortisone butyrate lotion. However, topical embryofetal development studies were conducted in rats and rabbits with a hydrocortisone butyrate ointment formulation. Topical doses of 1% and 10% hydrocortisone butyrate ointment were administered to pregnant female rats during gestation days 6 to 15 or pregnant female rabbits during gestation days 6 to 18. A dose- dependent increase in fetal resorptions was noted in rabbits (0.2 to 2X MTHD) and fetal resorptions were noted in rats at the 10% hydrocortisone butyrate ointment dose (80X MTHD). No treatment-related effects on embyrofetal toxicity were noted at the 1% hydrocortisone butyrate ointment dose in rats (8 MTHD). A dose at which no treatment- related effects on embryofetal toxicity were observed in rabbits after topical administration of hydrocortisone butyrate ointment was not established in this study. No treatment-related effects on teratogenicity were noted at a dose of 10% hydrocortisone butyrate ointment in rats or rabbits (80X MTHD and 2X MTHD, respectively).

A peri- and post-natal development study was conducted in rats. Subcutaneous doses of 0.6, 1.8 and 5.4 mg/kg/day hydrocortisone butyrate were administered to pregnant female rats from gestation day 6 – lactation day 20. In the presence of maternal toxicity, a dose- dependent decrease in fetal weight was noted at doses ≥ 1.8 mg/kg/day (0.7X MTHD). No treatment-related effects on fetal toxicity were noted at 0.6 mg/kg/day (0.2X MTHD). A delay in sexual maturation was noted at 5.4 mg/kg/day (2X MTHD). No treatment-related effects on sexual maturation were noted at 1.8 mg/kg/day. No treatment-related effects on behavioral development or subsequent reproductive performance were noted at 5.4 mg/kg/day.

8.3 Nursing Mothers

Systemically administered corticosteroids appear in human milk and could suppress growth, interfere with endogenous corticosteroid production, or cause other untoward effects. It is not known whether topical administration of corticosteroids could result in sufficient systemic absorption to produce detectable quantities in human milk. Because many drugs are excreted in human milk, caution should be exercised when hydrocortisone butyrate lotion is administered to a nursing woman.

8.4 Pediatric Use

Safety and efficacy in pediatric patients below 3 months of age have not been established.

Because of higher skin surface-to-body-mass ratios, pediatric patients are at a greater risk than adults of HPA axis suppression when they are treated with topical corticosteroids [see WARNINGS AND PRECAUTIONS (5.1)]. They are therefore also at a greater risk of glucocorticosteroid insufficiency after withdrawal of treatment and of Cushing's syndrome while on treatment.

Eighty-four (84) pediatric subjects (3 months to less than 18 years of age) with moderate to severe atopic dermatitis affecting at least 25% of body surface area (BSA) treated with hydrocortisone butyrate lotion three times daily for up to 4 weeks were assessed for HPA axis suppression. The disease severity (moderate to severe atopic dermatitis) and the dosing regimen (three times daily) in this HPA axis study were different from the subject population (mild to moderate atopic dermatitis) and the dosing regimen (two times daily) for which hydrocortisone butyrate lotion is indicated. Seven of the 82 evaluable subjects (8.5%) demonstrated laboratory evidence of suppression, where the sole criterion for defining HPA axis suppression was a serum cortisol level of less than or equal to 18 micrograms per deciliter after cosyntropin stimulation. Suppressed subjects ranged in age from 1 to 12 years and, at the time of enrollment, had 35% to 90% BSA involvement. These subjects did not develop any other signs or symptoms of HPA axis suppression. At the first follow up visit, approximately one month after the conclusion of treatment, cosyntropin stimulation results of all subjects had returned to normal, with the exception of one subject. This last subject recovered adrenal function by the second post treatment visit, 55 days post-treatment.

Cushing's syndrome, linear growth retardation, delayed weight gain, and intracranial hypertension have also been reported in pediatric patients receiving topical corticosteroids. Manifestations of adrenal suppression in pediatric patients include low plasma cortisol levels to an absence of response to ACTH stimulation. Manifestations of intracranial hypertension include bulging fontanelles, headaches, and bilateral papilledema.

8.5 Geriatric Use

Clinical studies of hydrocortisone butyrate lotion did not include sufficient numbers of subjects aged 65 and over to determine whether they respond differently from younger subjects.

11 DESCRIPTION

Hydrocortisone butyrate lotion, 0.1% contains hydrocortisone butyrate, a non- fluorinated hydrocortisone ester, for topical use. The chemical name of hydrocortisone butyrate is 11β,17,21-Trihydroxypregn-4-ene-3,20-dione 17-butyrate. It has the following structural formula:

Hydrocortisone butyrate USP is a white crystalline powder with a molecular weight of 432.56, and a molecular formula of C25H36O6. It is practically insoluble in water, slightly soluble in ether, soluble in methanol, in alcohol, and in acetone, and freely soluble in chloroform.

Each gram of hydrocortisone butyrate lotion, 0.1% contains 1 mg of hydrocortisone butyrate USP in a white to off white lotion base consisting of butylated hydroxytoluene, butylparaben, ceteth-20, cetostearyl alcohol, citric acid monohydrate, light mineral oil, propylparaben, purified water, sodium citrate, and white petrolatum.

12 CLINICAL PHARMACOLOGY

12.1 Mechanism of Action

Topical corticosteroids share anti-inflammatory, antipruritic, and vasoconstrictive properties. The mechanism of the anti-inflammatory activity of the topical corticosteroids is unclear. However, corticosteroids are thought to act by the induction of phospholipase A2 inhibitory proteins, collectively called lipocortins. It is postulated that these proteins control the biosynthesis of potent mediators of inflammation such as prostaglandins and leukotrienes by inhibiting the release of their common precursor, arachidonic acid. Arachidonic acid is released from membrane phospholipids by phospholipase A2.

12.3 Pharmacokinetics

No studies were conducted to determine the pharmacokinetics of hydrocortisone butyrate lotion.

The extent of percutaneous absorption of topical corticosteroids is determined by many factors, including the vehicle, the integrity of the epidermal barrier, and the use of occlusive dressings.

Topical corticosteroids can be absorbed through normal intact skin. Inflammation and/or other disease processes in the skin, occlusive dressings, or widespread application may increase percutaneous absorption.

Once absorbed through the skin, topical corticosteroids are handled through pharmacokinetic pathways similar to systemically administered corticosteroids.

13 NONCLINICAL TOXICOLOGY

13.1 Carcinogenesis, Mutagenesis, Impairment of Fertility

In a 2-year dermal rat carcinogenicity study with hydrocortisone butyrate lotion, hydrocortisone butyrate was administered to Sprague-Dawley rats at topical doses of 0.05, 0.15, and 0.3 mg/kg/day in males and 0.1, 0.25, and 0.5 mg/kg/day in females (0.1% lotion). No drug-related tumors were noted in this study up to the highest doses evaluated in this study of 0.3 mg/kg/day in males (0.1X MTHD) and 0.5 mg/kg/day in females (0.2X MTHD).

Hydrocortisone butyrate revealed no evidence of mutagenic or clastogenic potential based on the results of two in vitro genotoxicity tests (Ames test and L5178Y/TK+/- mouse lymphoma assay) and one in vivo genotoxicity test (mouse micronucleus assay).

No evidence of impairment of fertility or effect on mating performance was observed in a fertility and general reproductive performance study conducted in male and female rats at subcutaneous doses up to and including 1.8 mg/kg/day (0.7X MTHD). Mild effects on maternal animals, such as reduced food consumption and a subsequent reduction in body weight gain, were seen at doses ≥ 0.6 mg/kg/day (0.2X MTHD).

14 CLINICAL STUDIES

In a multicenter, randomized, vehicle-controlled trial of 284 pediatric subjects 3 months to 18 years of age with mild to moderate atopic dermatitis, hydrocortisone butyrate lotion or vehicle was applied twice daily for up to four weeks. Treatment success was assessed at day 29 (after 28 days of treatment) and was defined as the proportion of patients who achieved both "clear" or "almost clear" and at least a two grade improvement from baseline on a 5-point Physician's Global Assessment (PGA) scale. Study results are shown in Table 3.

TABLE 3. Efficacy results at Day 29 in pediatric subjects
 | Hydrocortisone butyrate lotion (n=139) | Vehicle (n=145)
Number (%) successes | 68 (49%) | 35 (24%)

Another multicenter, randomized, double-blind study compared twice daily treatment with hydrocortisone butyrate lotion (n=151) to vehicle (n=150) for three or four weeks in adult subjects (ages 18 years or older) having atopic dermatitis, including those with mild or moderate severity. Results favored hydrocortisone butyrate lotion over vehicle.

16 HOW SUPPLIED/STORAGE AND HANDLING

Hydrocortisone butyrate lotion, 0.1%, is white to off white in color and supplied in bottles of 2 fl. oz. (NDC 68180-951-01) and 4 fl. oz. (NDC 68180-951-02).

Store at 25°C (77°F); excursions permitted to 15° to 30°C (59° to 86°F) [see USP Controlled Room Temperature]. Protect from freezing.

17 PATIENT COUNSELING INFORMATION

Patients using hydrocortisone butyrate lotion should receive the following information and instructions:

- Apply a thin layer to the affected skin two times daily, and rub in gently.
- Discontinue hydrocortisone butyrate lotion when control is achieved.
- Do not use for longer than 4 weeks.
- Avoid contact with the eyes.
- Do not bandage, otherwise cover, or wrap the affected skin area so as to be occlusive unless directed by physician.
- Do not use hydrocortisone butyrate lotion in the diaper area, as diapers or plastic pants may constitute occlusive dressings.
- Do not use hydrocortisone butyrate lotion on the face, underarms, or groin areas unless directed by physician.
- If no improvement is seen within 2 weeks, contact physician.
- Do not use other corticosteroid -containing products while using hydrocortisone butyrate lotion without first consulting physician.

Rx only

LUPIN and the are registered trademarks of Lupin Pharmaceuticals, Inc

Manufactured for:

Lupin Pharmaceuticals, Inc.

Naples, FL 34108

United States

Manufactured by:

Lupin Limited

Pithampur (M.P.) - 454 775

India

October 2024 ID#: 277876

PACKAGE LABEL

Hydrocortisone Butyrate Lotion, 0.1%

4 fl oz (118 mL)- Bottle label

NDC 68180-951-02

Rx only

Hydrocortisone Butyrate Lotion, 0.1%

4 fl oz (118 mL)- Carton label

NDC 68180-951-02

Rx only